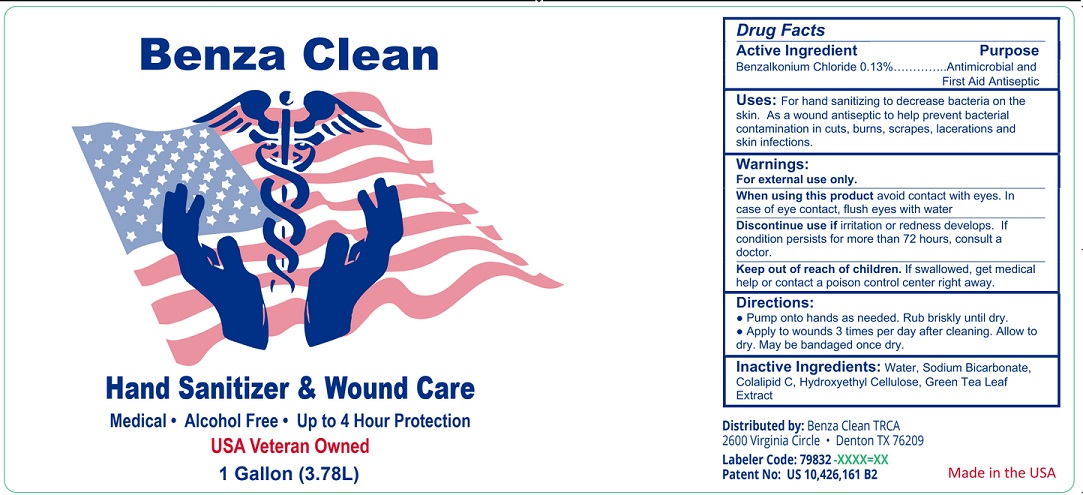 DRUG LABEL: Benza Clean hand sanitizer
NDC: 79832-001 | Form: LIQUID
Manufacturer: BIOSYN INC
Category: otc | Type: HUMAN OTC DRUG LABEL
Date: 20200926

ACTIVE INGREDIENTS: BENZALKONIUM CHLORIDE 1.3 mg/1 mL
INACTIVE INGREDIENTS: WATER; SODIUM BICARBONATE; COCAMIDOPROPYL PROPYLENE GLYCOL-DIMONIUM CHLORIDE PHOSPHATE; HYDROXYETHYL CELLULOSE, UNSPECIFIED; GREEN TEA LEAF

Active Ingredient

Benzalkonium Chloride 0.13%

Purpose

Antimicrobial and First Aid Antiseptic

Uses

For hand sanitizing to decrease bacteria on the skin. As a wound antiseptic to help prevent bacterial contamination in cuts, burns, scrapes, lacerations and skin infections.

Warnings

For external use only.

When using this product avoid contact with eyes. Incase of eye contact, flush eyes with water.
Discontinue useif irritation or redness develops. If condition persists for more than 72 hours, consult a doctor.

Keep out of reach of children. If swallowed, get medical help or contact a Poison Control Center right away.

Directions

- Pump onto hands as needed. Rub briskly until dry.
- Apply to wounds 3 times per day after cleaning. Allow to dry. May be bandaged once dry.

Other information

- Store between 15-30C (59-86F)
- Avoid freezing and excessive heat above 40C (104F)

Inactive ingredients

Water, Sodium Bicarbonate, Colalipid C, Hydroxyethyl Cellulose, Green Tea Leaf Extract.